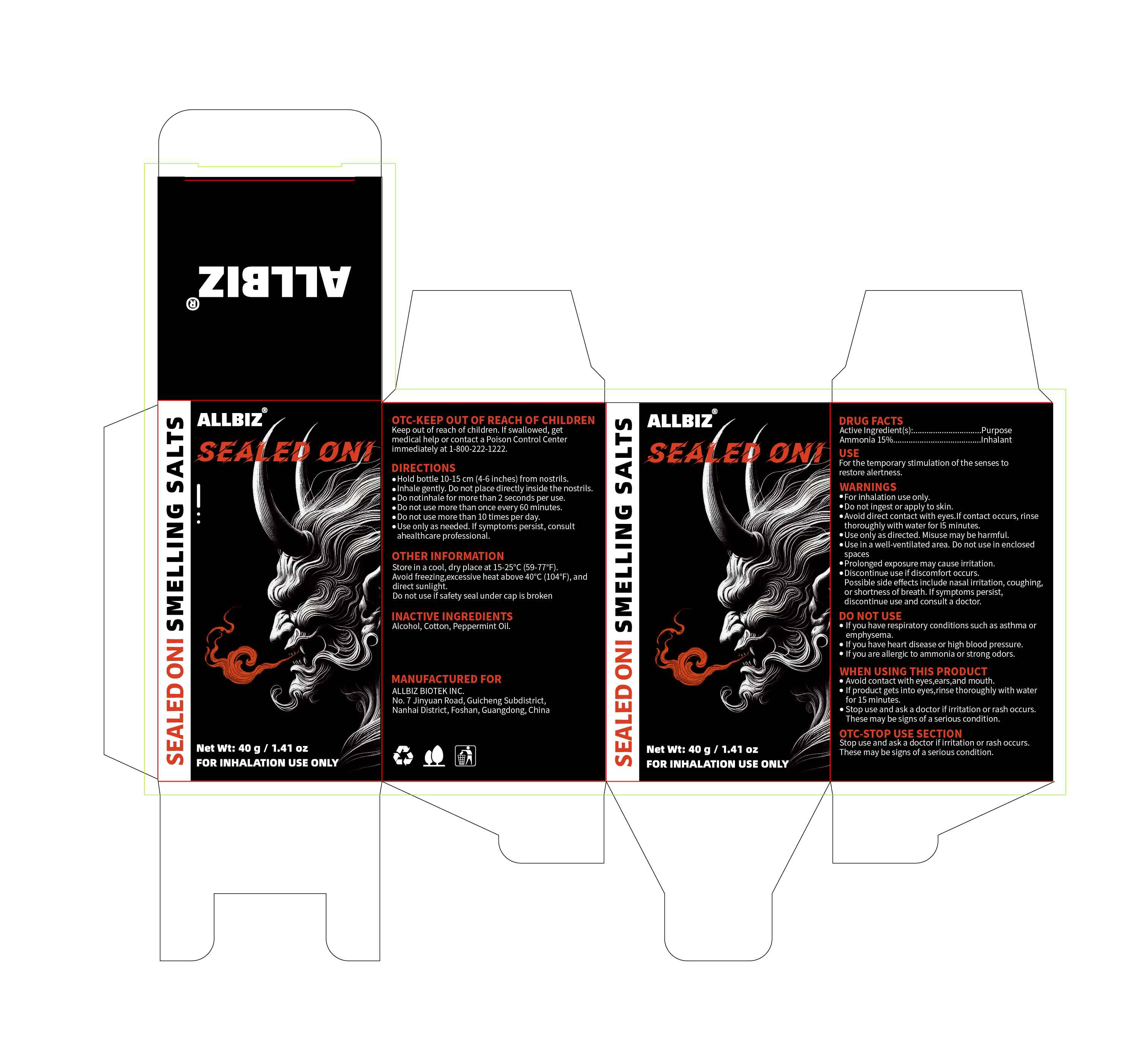 DRUG LABEL: ALLBIZ SEALED ONI SMELLING SALTS
NDC: 85920-001 | Form: GAS
Manufacturer: Foshan Nanhai District Didi Didi E Commerce Co., Ltd.
Category: otc | Type: HUMAN OTC DRUG LABEL
Date: 20250720

ACTIVE INGREDIENTS: AMMONIA 0.15 g/1 g
INACTIVE INGREDIENTS: ALCOHOL; COTTON; PEPPERMINT OIL

ACTIVE INGREDIENT

Ammonia (15%)

PURPOSE

Inhalant

INDICATIONS AND USAGE

For the temporary stimulation of the senses to restore alertness

DOSAGE AND ADMINISTRATION

Hold bottle 10-15 cm(4-6 inches) from nostrils.Inhale gently. Do not place directly inside the nostrils.Do notinhale for more than 2 seconds per use,Do not use more than once every 60 minutes.Do not use more than 1l0 times per day.Use only as needed. lfsymptoms persist, consultahealthcare professional.

Keep out of reach of children.lf swallowed, getmedical help or contact a Poison Control Centerimmediately at 1-800-222-1222.

WARNINGS

For inhalation use only.Do not ingest or apply to skin.Avoid direct contact with eyes.lf contact occurs, rinsethoroughly with water for l5 minutes.Use only as directed. Misuse may be harmful.Use in a well-ventilated area. Do not use in enclosed
spacesProlonged exposure may cause irritation.Discontinue use if discomfort occurs.Possible side effects include nasal irritation, coughingor shortness of breath.lfsymptoms persist,discontinue use and consult a doctor.

DO NOT USE

lf you have respiratory conditions such as asthma oremphysema.lf you have heart disease or high blood pressure.lf you are allergic to ammonia or strong odors.

WHEN USING

Avoid contact with eyes,ears,and mouth.lf product gets into eyes,rinse thoroughly with waterfor 15 minutes.Stop use and ask a doctor if irritation or rash occurs.These may be signs of a serious condition.

Stop use and ask a doctor if irritation or rash occursThese may be signs of a serious condition.

OTHER SAFETY INFORMATION

Store in a cool, dry place at 15-25°C (59-77°F).Avoid freezing,excessive heat above 40°C (104°F),anddirect sunlight.Do not use if safety seal under cap is broken

INACTIVE INGREDIENT

Alcohol, Cotton, Peppermint Oil.